DRUG LABEL: Unknown
Manufacturer: Baxter Healthcare Corporation
Category: prescription | Type: HUMAN PRESCRIPTION DRUG LABELING
Date: 20060510

PLASMA-LYTE R Injection (Multiple Electrolytes Injection, Type 2, USP)
in VIAFLEX Plastic Container

DESCRIPTION

PLASMA-LYTE R Injection (Multiple Electrolytes Injection, Type 2, USP) is a sterile, nonpyrogenic isotonic solution in a single dose container for intravenous administration. Each 100 mL contains 640 mg of Sodium Acetate Trihydrate, USP (C2H3NaO2•3H2O); 496 mg of Sodium Chloride, USP (NaCl); 89.6 mg of Sodium Lactate (C3H5NaO3); 74.6 mg of Potassium Chloride, USP (KCl); 36.8 mg of Calcium Chloride, USP (CaCl2•2H2O); and 30.5 mg of Magnesium Chloride, USP (MgCl2•6H2O). It contains no antimicrobial agents. The pH is adjusted with hydrochloric acid. The pH is 5.5 (4.0 to 8.0).

PLASMA-LYTE R Injection (Multiple Electrolytes Injection, Type 2, USP) administered intravenously has value as a source of water, electrolytes, and calories. One liter has an ionic concentration of 140 mEq sodium, 10 mEq potassium, 5 mEq calcium, 3 mEq magnesium, 103 mEq chloride, 47 mEq acetate, and 8 mEq lactate. The osmolarity is 312 mOsmol/L (calc). Normal physiologic osmolarity range is approximately 280 to 310 mOsmol/L. Administration of substantially hypertonic solutions may cause vein damage. The caloric content is 11 kcal/L.

The VIAFLEX plastic container is fabricated from a specially formulated polyvinyl chloride (PL 146 Plastic). The amount of water that can permeate from inside the container into the overwrap is insufficient to affect the solution significantly. Solutions in contact with the plastic container can leach out certain of its chemical components in very small amounts within the expiration period, e.g., di-2-ethylhexyl phthalate (DEHP), up to 5 parts per million. However, the safety of the plastic has been confirmed in tests in animals according to USP biological tests for plastic containers as well as by tissue culture toxicity studies.

CLINICAL PHARMACOLOGY

PLASMA-LYTE R Injection (Multiple Electrolytes Injection, Type 2, USP) has value as a source of water and electrolytes. It is capable of inducing diuresis depending on the clinical condition of the patient.

PLASMA-LYTE R Injection (Multiple Electrolytes Injection, Type 2, USP) produces a metabolic alkalinizing effect. Acetate and lactate ions are metabolized ultimately to carbon dioxide and water, which requires the consumption of hydrogen cations.

INDICATIONS AND USAGE

PLASMA-LYTE R Injection (Multiple Electrolytes Injection, Type 2, USP) is indicated as a source of water and electrolytes or as an alkalinizing agent.

CONTRAINDICATIONS

None known

WARNINGS

PLASMA-LYTE R Injection (Multiple Electrolytes Injection, Type 2, USP) should be used with great care, if at all, in patients with congestive heart failure, severe renal insufficiency and in clinical states in which there exists edema with sodium retention.

PLASMA-LYTE R Injection (Multiple Electrolytes Injection, Type 2, USP) should be used with great care, if at all, in patients with hyperkalemia, severe renal failure and in conditions in which potassium retention is present.

PLASMA-LYTE R Injection (Multiple Electrolytes Injection, Type 2, USP) should be used with great care in patients with metabolic or respiratory alkalosis. The administration of lactate or acetate ions should be done with great care in those conditions in which there is an increased level or an impaired utilization of these ions, such as severe hepatic insufficiency. PLASMA-LYTE R Injection (Multiple Electrolytes Injection, Type 2, USP) should not be administered simultaneously with blood through the same administration set because of the likelihood of coagulation.

The intravenous administration of PLASMA-LYTE R Injection (Multiple Electrolytes Injection, Type 2, USP) can cause fluid and/or solute overloading resulting in dilution of serum electrolyte concentrations, overhydration, congested states or pulmonary edema. The risk of dilutional states is inversely proportional to the electrolyte concentrations of the injection. The risk of solute overload causing congested states with peripheral and pulmonary edema is directly proportional to the electrolyte concentrations of the injection.

In patients with diminished renal function, administration of PLASMA-LYTE R Injection (Multiple Electrolytes Injection, Type 2, USP) may result in sodium or potassium retention. PLASMA-LYTE R Injection (Multiple Electrolytes Injection, Type 2, USP) is not for use in the treatment of lactic acidosis.

PRECAUTIONS

Clinical evaluation and periodic laboratory determinations are necessary to monitor changes in fluid balance, electrolyte concentrations and acid base balance during prolonged parenteral therapy or whenever the condition of the patient warrants such evaluation.

PLASMA-LYTE R Injection (Multiple Electrolytes Injection, Type 2, USP) should be used with caution. Excess administration may result in metabolic alkalosis.

Caution must be exercised in the administration of PLASMA-LYTE R Injection (Multiple Electrolytes Injection, Type 2, USP) to patients receiving corticosteroids or corticotropin.

Pregnancy

Teratogenic Effects

Pregnancy Category C

Animal reproduction studies have not been conducted with PLASMA-LYTE R Injection (Multiple Electrolytes Injection, Type 2, USP). It is also not known whether PLASMA-LYTE R Injection (Multiple Electrolytes Injection, Type 2, USP) can cause fetal harm when administered to a pregnant woman or can affect reproduction capacity. PLASMA-LYTE R Injection (Multiple Electrolytes Injection, Type 2, USP) should be given to a pregnant woman only if clearly needed.

Pediatric Use

Safety and effectiveness of PLASMA-LYTE R Injection (Multiple Electrolytes Injection, Type 2, USP) in pediatric patients have not been established by adequate and well controlled trials, however, the use of electrolyte solutions in the pediatric population is referenced in the medical literature. The warnings, precautions and adverse reactions identified in the label copy should be observed in the pediatric population.

Geriatric Use

Clinical studies of PLASMA-LYTE R Injection (Multiple Electrolytes Injection, Type 2, USP) did not include sufficient numbers of subjects aged 65 and over to determine whether they respond differently from younger subjects. Other reported clinical experience has not identified differences in responses between the elderly and younger patients. In general, dose selection for an elderly patient should be cautious, usually starting at the low end of the dosing range, reflecting the greater frequency of decreased hepatic, renal, or cardiac function, and of concomitant disease or drug therapy.

Do not administer unless solution is clear and seal is intact.

ADVERSE REACTIONS

Reactions which may occur because of the solution or the technique of administration include febrile response, infection at the site of injection, venous thrombosis or phlebitis extending from the site of injection, extravasation and hypervolemia.

If an adverse reaction does occur, discontinue the infusion, evaluate the patient, institute appropriate therapeutic countermeasures and save the remainder of the fluid for examination if deemed necessary.

DOSAGE AND ADMINISTRATION

As directed by a physician. Dosage is dependent upon the age, weight and clinical condition of the patient as well as laboratory determinations.

Parenteral drug products should be inspected visually for particulate matter and discoloration prior to administration whenever solution and container permit.

All injections in VIAFLEX plastic containers are intended for intravenous administration using sterile equipment.

Additives may be incompatible. Complete information is not available. Those additives known to be incompatible should not be used. Consult with pharmacist, if available. If, in the informed judgment of the physician, it is deemed advisable to introduce additives, use aseptic technique. Mix thoroughly when additives have been introduced. Do not store solutions containing additives.

HOW SUPPLIED

PLASMA-LYTE R Injection (Multiple Electrolytes Injection, Type 2, USP) in VIAFLEX plastic containers is available as shown below:

Code | Size (mL) | NDC
2B2504 | 1000 | NDC 0338-0177-04

Exposure of pharmaceutical products to heat should be minimized. Avoid excessive heat. It is recommended the product be stored at room temperature (25°C); brief exposure up to 40°C does not adversely affect the product.

DIRECTIONS FOR USE OF VIAFLEX PLASTIC CONTAINER

Warning: Do not use plastic containers in series connections. Such use could result in air embolism due to residual air being drawn from the primary container before administration of the fluid from the secondary container is completed.

To Open

Tear overwrap down side at slit and remove solution container. Some opacity of the plastic due to moisture absorption during the sterilization process may be observed. This is normal and does not affect the solution quality or safety. The opacity will diminish gradually. Check for minute leaks by squeezing inner bag firmly. If leaks are found, discard solution as sterility may be impaired. If supplemental medication is desired, follow directions below.

Preparation for Administration

1. Suspend container from eyelet support.

2. Remove plastic protector from outlet port at bottom of container.

3. Attach administration set. Refer to complete directions accompanying set.

To Add Medication

Warning: Additives may be incompatible.

To add medication before solution administration

1. Prepare medication site.

2. Using syringe with 19 to 22 gauge needle, puncture resealable medication port and inject.

3. Mix solution and medication thoroughly. For high density medication such as potassium chloride, squeeze ports while ports are upright and mix thoroughly.

To add medication during solution administration

1. Close clamp on the set.

2. Prepare medication site.

3. Using syringe with 19 to 22 gauge needle, puncture resealable medication port and inject.

4. Remove container from IV pole and/or turn to an upright position.

5. Evacuate both ports by squeezing them while container is in the upright position.

6. Mix solution and medication thoroughly.

7. Return container to in use position and continue administration.

Baxter Healthcare Corporation

Deerfield, IL 60015 USA

Printed in USA

©Copyright 1982, 1983, 1984, 1989, 1993, Baxter Healthcare Corporation.

All rights reserved.

7-19-29-403

BAXTER, PLASMA-LYTE, VIAFLEX, AND PL 146 ARE TRADEMARKS OF BAXTER INTERNATIONAL INC.